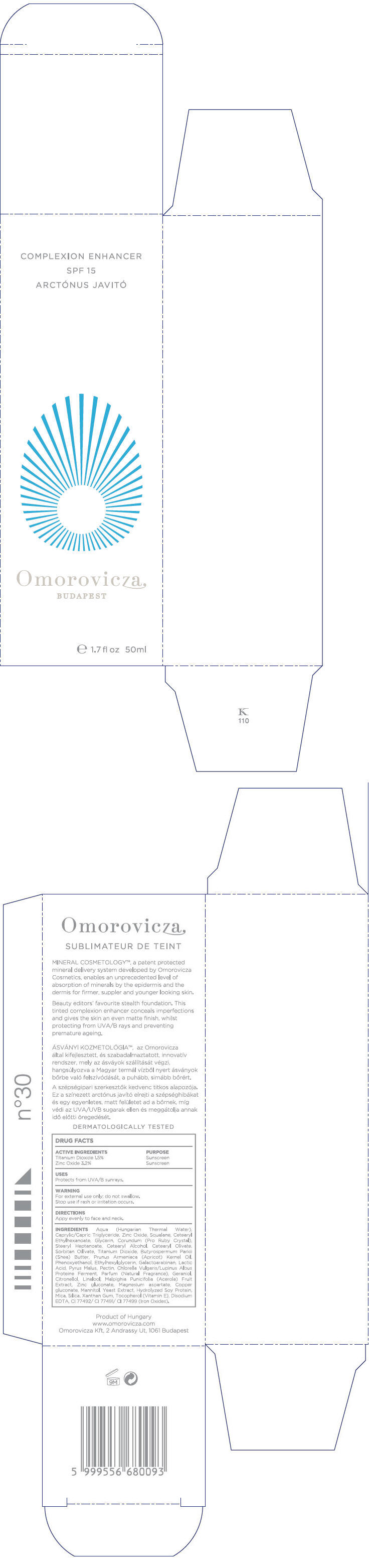 DRUG LABEL: Complexion Enhancer SPF15
NDC: 41442-110 | Form: CREAM
Manufacturer: Omorovicza Kozmetikai Kft.
Category: otc | Type: HUMAN OTC DRUG LABEL
Date: 20110301

ACTIVE INGREDIENTS: Titanium dioxide 0.75 mL/50 mL; Zinc oxide 1.6 mL/50 mL
INACTIVE INGREDIENTS: Caprylic/Capric Mono/Diglycerides; Squalane; Cetearyl Ethylhexanoate; Glycerin; Aluminum Oxide; Stearyl Heptanoate; Cetostearyl Alcohol; Cetearyl Olivate; Sorbitan Olivate; Shea Butter; Apricot Seed Oil; Phenoxyethanol; Ethylhexylglycerin; Lactic Acid; Apple; Pectin; Geraniol; .BETA.-CITRONELLOL, (+/-)-; LINALOOL, (+)-; Acerola; Zinc Gluconate; Magnesium Aspartate; Copper Gluconate; Mannitol; Yeast; Soy Protein; Mica; Silicon Dioxide; Xanthan Gum; Alpha-Tocopherol; Edetate Disodium; Ferrosoferric Oxide

Complexion Enhancer SPF15

DRUG FACTS

ACTIVE INGREDIENT

ACTIVE INGREDIENTS | PURPOSE
Titanium Dioxide 1.5% | Sunscreen
Zinc Oxide 3.2% | Sunscreen

USES

Protects from UVA/B sunrays

WARNING

For external use only; do not swallow.

Stop use if rash or irritation occurs.

DIRECTIONS

Apply evenly to face and neck.

INGREDIENTS

Aqua (Hungarian Thermal Water), Caprylic/Capric Triglyceride, Zinc Oxide, Squalane, Cetearyl Ethylhexanoate, Glycerin, Corundum (Pro Ruby Crystal), Stearyl Heptanoate, Cetearyl Alcohol, Cetearyl Olivate, Sorbitan Olivate, Titanium Dioxide, Butyrospermum Parkii (Shea) Butter, Prunus Armeniaca (Apricot) Kernel Oil, Phenoxyethanol, Ethylhexylglycerin, Galactoarabinan, Lactic Acid, Pyrus Malus, Pectin, Chlorella Vulgaris/Lupinus Albus Protein Ferment, Parfum (Fragrance), Geraniol, Citronellol, Linalool, Malpighia Punicifolia (Acerola) Fruit Extract, Zinc gluconate, Magnesium aspartate, Copper gluconate, Mannitol, Yeast Extract, Hydrolyzed Soy Protein, Mica, Silica, Xanthan Gum, Tocopherol (Vitamin E), Disodium EDTA, CI 77492/ CI 77491/ CI 77499 (Iron Oxides)

PRINCIPAL DISPLAY PANEL - 50ml Bottle Carton

COMPLEXION ENHANCER
SPF 15
ARCTÓNUS JAVITÓ

Omorovicza
BUDAPEST

e 1.7 fl oz 50ml